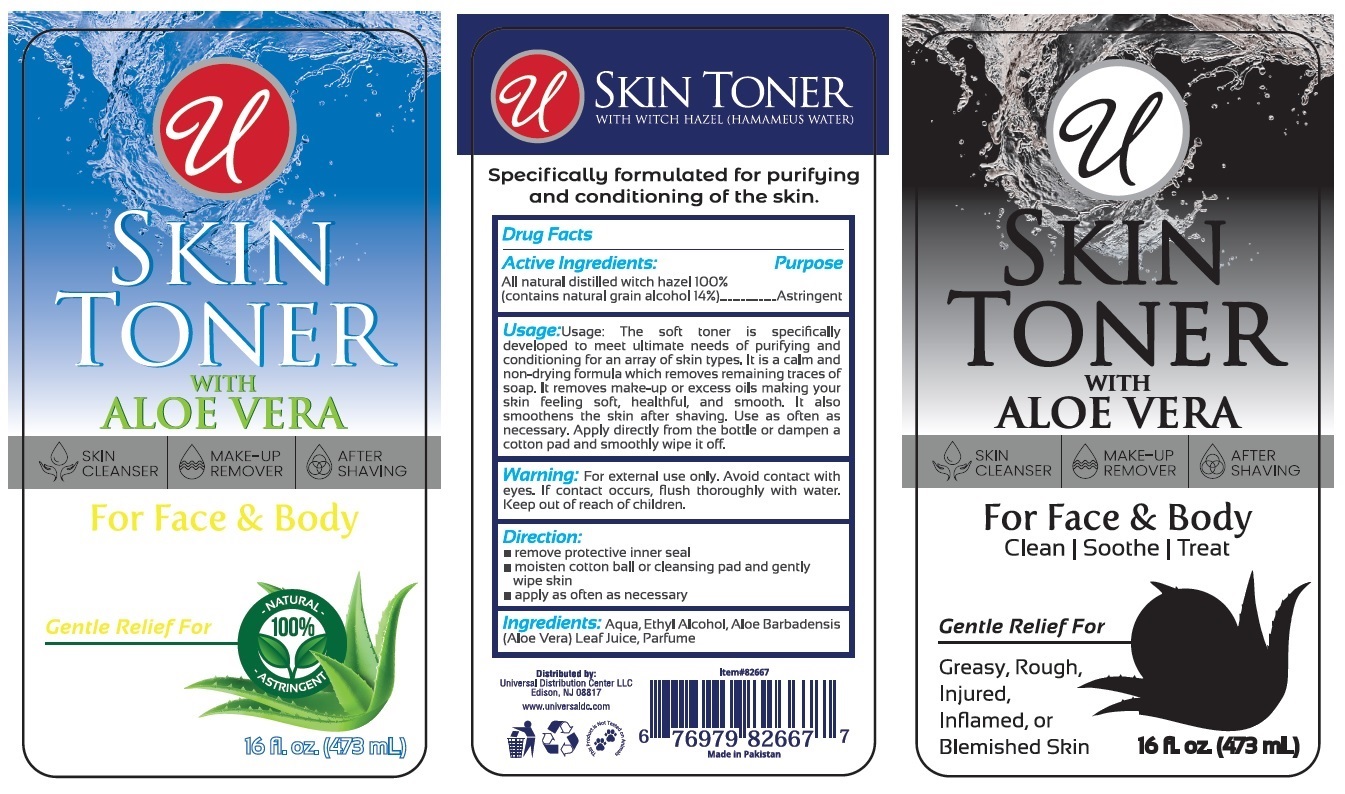 DRUG LABEL: SKIN TONER
NDC: 79982-004 | Form: LIQUID
Manufacturer: STANCOS (PRIVATE) LIMITED
Category: otc | Type: HUMAN OTC DRUG LABEL
Date: 20210104

ACTIVE INGREDIENTS: WITCH HAZEL 14 g/100 mL
INACTIVE INGREDIENTS: WATER; ALCOHOL; ALOE VERA LEAF

SKIN TONER

Active Ingredients:

All natural distilled witch hazel 100%

(contains natural grain alcohol 14%)

Purpose

Astringent

Usage:

The soft toner is specifically developed to meet ultimate needs of purifying and conditioning for an array of skin types. It is a calm and non-drying formula which removes remaining traces of soap. It removes make-up or excess oils making your skin feeling soft, healthful, and smooth. It also smoothens the skin after shaving. Use as often as necessary. Apply directly from the bottle or dampen a cotton pad and smoothly wipe it off.

Warning:

For external use only. Avoid contact with eyes. If contact occurs, flush thoroughly with water.

Keep out of reach of children.

Direction:

• remove protective inner seal

• moisten cotton ball or cleansing pad and gently wipe skin

• apply as often as necessary

Ingredients:

Aqua, Ethyl Alcohol, Aloe Barbadensis (Aloe Vera) Leaf Juice, Parfum

WITH ALOE VERA

SKIN CLEANSER

MAKE-UP REMOVER

AFTER SHAVING

For Face & Body

Clean | Soothe | Treat

Gentle Relief For

Greasy, Rough, Injured, Inflamed, or Blemished Skin

NATURAL 100%

WITH WITCH HAZEL (HAMAMEUS WATER)

Specifically formulated for purifying and conditioning of the skin.

Distributed by:

Universal Distribution Centre LLC

Edison, NJ 08817

www.universaldc.com

Made in Pakistan